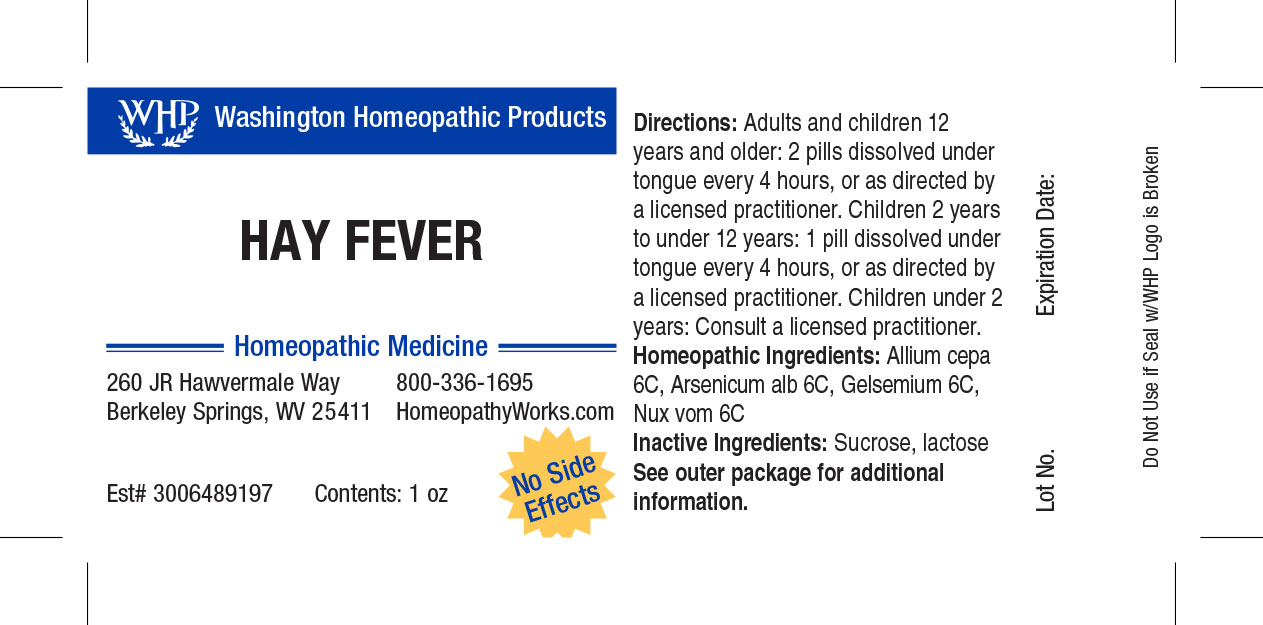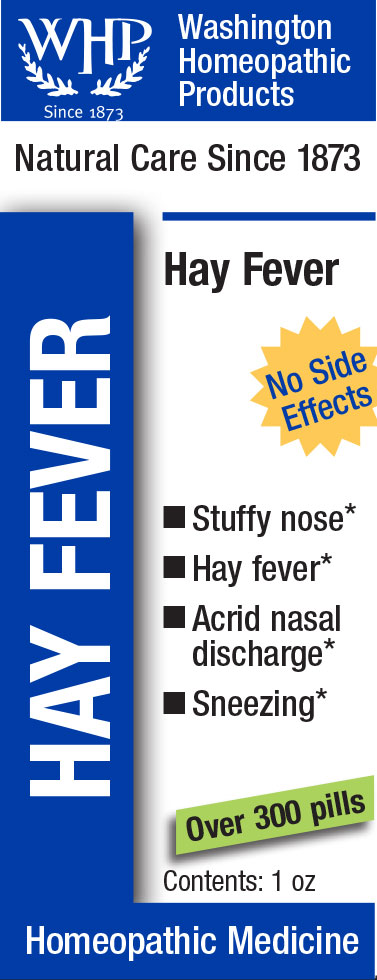 DRUG LABEL: WHP Hay Fever
NDC: 71919-807 | Form: PELLET
Manufacturer: Washington Homeopathic Products
Category: homeopathic | Type: HUMAN OTC DRUG LABEL
Date: 20250128

ACTIVE INGREDIENTS: GELSEMIUM SEMPERVIRENS ROOT 6 [hp_C]/1 1; STRYCHNOS NUX-VOMICA SEED 6 [hp_C]/1 1; ARSENIC TRIOXIDE 6 [hp_C]/1 1; ONION 6 [hp_C]/1 1
INACTIVE INGREDIENTS: LACTOSE; SUCROSE

WHP Hay Fever

ACTIVE INGREDIENTS

ALLIUM CEPA 6C

ARSENICUM ALB 6C

GELSEMIUM 6C

NUX VOM 6C

USES

Temporarily relieves symptoms associated with hay fever.

KEEP OUT OF REACH OF CHILDREN

As with all medications, keep out of reach of children.

INDICATIONS

ALLIUM CEPA Head cold

ARSENICUM ALB Vomiting

GELSEMIUM Lethargy

NUX VOM Vomiting

STOP USE AND ASK DOCTOR

If symptoms persist or recur, discontinue use. If pregnant or nursing, consult a licensed practitioner before using this product.

DIRECTIONS

Directions: Adults and children 12 years and older: 2 pills dissolved under tongue every 4 hours, or as directed by a licensed practitioner. Children 4 years to under 12 years: 1 pill dissolved under tongue every 4 hours, or as directed by a licensed practitioner. Children under 4 years: Consult a licensed practitioner.

INACTIVE INGREDIENTS

Sucrose/Lactose